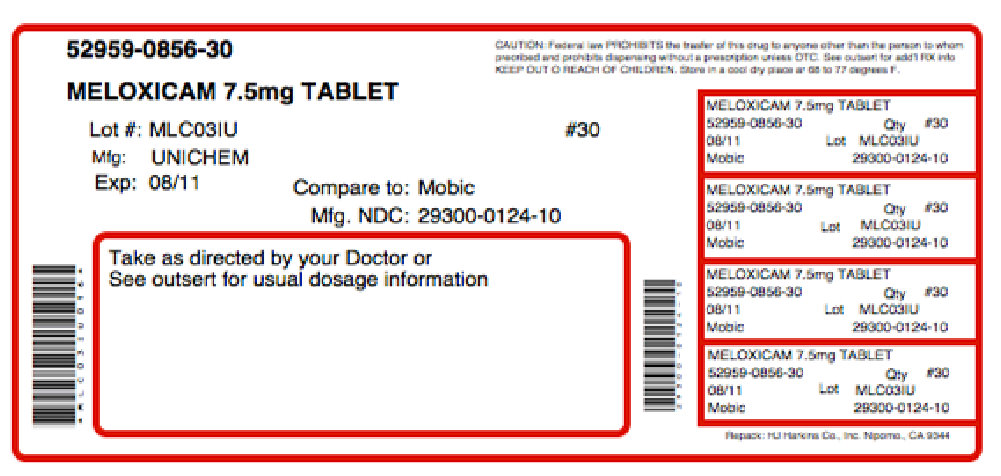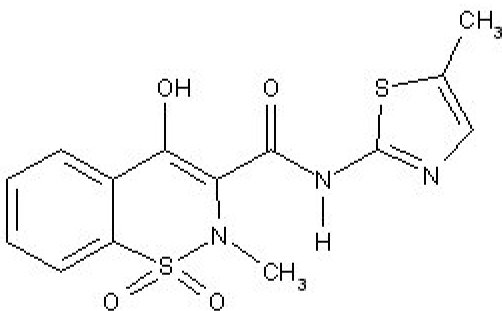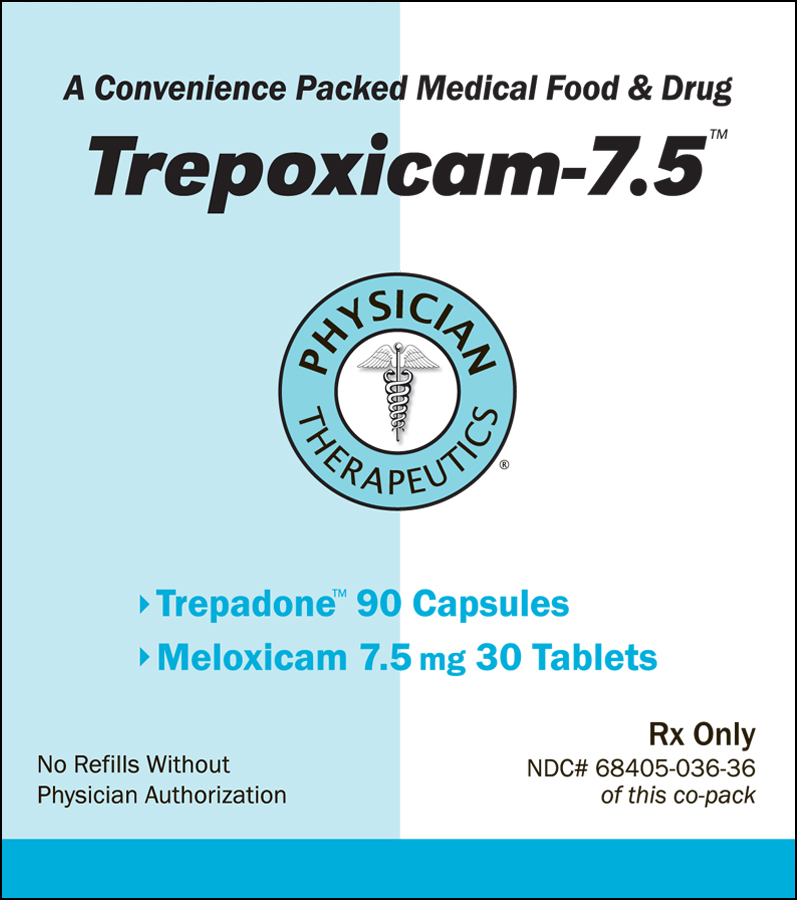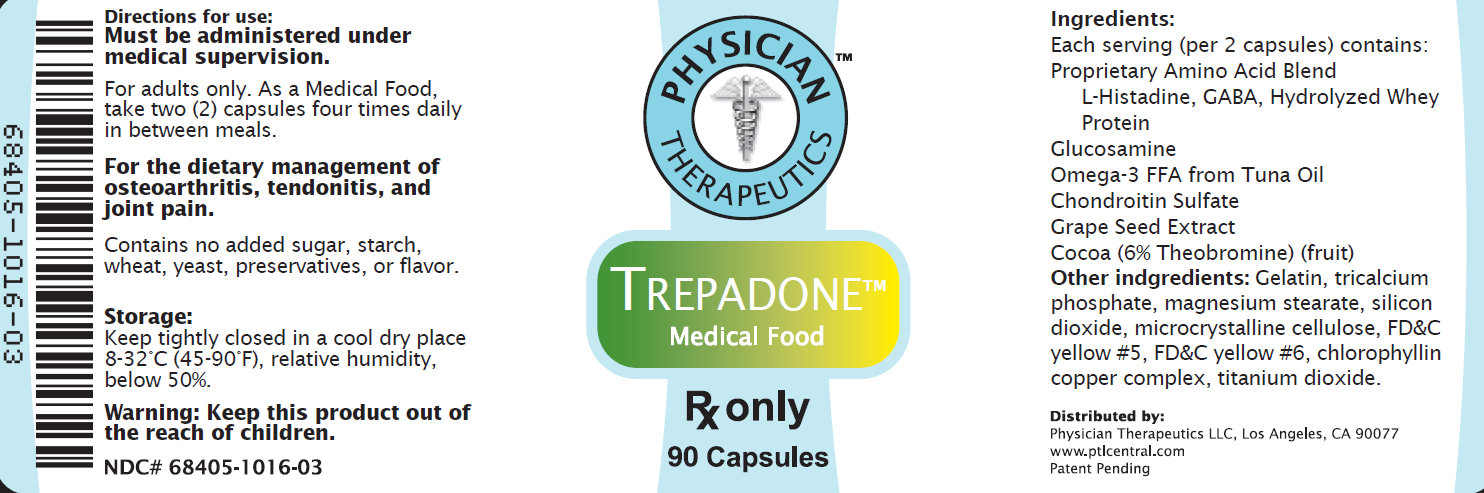 DRUG LABEL: Trepoxicam-7.5
NDC: 68405-036 | Form: KIT | Route: ORAL
Manufacturer: Physician Therapeutics LLC
Category: prescription | Type: HUMAN PRESCRIPTION DRUG LABEL
Date: 20110801

ACTIVE INGREDIENTS: MELOXICAM 7.5 mg/1 1; HISTIDINE 50 mg/1 1
INACTIVE INGREDIENTS: CROSPOVIDONE; LACTOSE MONOHYDRATE; MAGNESIUM STEARATE; CELLULOSE, MICROCRYSTALLINE; POVIDONE; TRISODIUM CITRATE DIHYDRATE; MAGNESIUM STEARATE; CELLULOSE, MICROCRYSTALLINE; MALTODEXTRIN; GELATIN

HIGHLIGHTS OF PRESCRIBING INFORMATION

Meloxicam 7.5 mg These highlights do not include all the information needed to use MOBIC safely and effectively. See full prescribing information for MOBIC. Mobic (meloxicam) tablets Mobic (meloxicam) oral suspension Initial U.S. Approval: 2000

BOXED WARNING

WARNING:

CARDIOVASCULAR and GASTROINTESTINAL RISKS

See full prescribing information for complete boxed warning. Cardiovascular Risk NSAIDs may cause an increased risk of serious cardiovascular thrombotic events, myocardial infarction, and stroke, which can be fatal. This risk may increase with duration of use. Patients with cardiovascular disease or risk factors for cardiovascular disease may be at greater risk. (5.1) MOBIC is contraindicated for the treatment of peri-operative pain in the setting of coronary artery bypass graft (CABG) surgery (4.2, 5.1) Gastrointestinal Risk NSAIDs cause an increased risk of serious gastrointestinal adverse events including bleeding, ulceration, and perforation of the stomach or intestines, which can be fatal. These events can occur at any time during use and without warning symptoms. Elderly patients are at greater risk for serious gastrointestinal events. (5.2)

INDICATIONS AND USAGE

MOBIC is a non-steroidal anti-inflammatory drug indicated for: Osteoarthritis (OA) (1.1) Rheumatoid Arthritis (RA) (1.2) Juvenile Rheumatoid Arthritis (JRA) in patients 2 years of age or older (1.3)

DOSAGE AND ADMINISTRATION

Use the lowest effective dose for the shortest duration consistent with individual treatment goals for the individual patient. OA (2.2) and RA (2.3): Starting dose: 7.5 mg once daily Dose may be increased to 15 mg once daily

JRA (2.4): 0.125 mg/kg once daily up to a maximum of 7.5 mg. JRA dosing using the oral suspension should be individualized based on the weight of the child. (2.4)

DOSAGE FORMS AND STRENGTHS

Tablets: 7.5 mg, 15 mg (3) Oral Suspension: 7.5 mg/5 mL (3)

CONTRAINDICATIONS

Known hypersensitivity (e.g., anaphylactoid reactions and serious skin reactions) to meloxicam (4.1) History of asthma, urticaria, or other allergic-type reactions after taking aspirin or other NSAIDs (4.1) Use during the peri-operative period in the setting of coronary artery bypass graft (CABG) surgery (4.2)

WARNINGS AND PRECAUTIONS

Serious and potentially fatal cardiovascular (CV) thrombotic events, myocardial infarction, and stroke. Patients with known CV disease/risk factors may be at greater risk. (5.1) Serious gastrointestinal (GI) adverse events which can be fatal. The risk is greater in patients with a prior history of ulcer disease or GI bleeding, and in patients at higher risk for GI events, especially the elderly. (5.2) Elevated liver enzymes, and rarely, severe hepatic reactions. Discontinue use immediately if abnormal liver enzymes persist or worsen. (5.3) New onset or worsening of hypertension. Blood pressure should be monitored closely during treatment. (5.4) Fluid retention and edema. Should be used with caution in patients with fluid retention or heart failure. (5.5) Renal papillary necrosis and other renal injury with long-term use. Use with caution in the elderly, those with impaired renal function, heart failure, liver dysfunction, and those taking diuretics, ACE-inhibitors, or angiotensin II antagonists. The use of MOBIC in patients with severe renal impairment is not recommended. (5.6) Serious skin adverse events such as exfoliative dermatitis, Stevens-Johnson syndrome (SJS), and toxic epidermal necrolysis (TEN), which can be fatal and can occur without warning. Discontinue MOBIC at first appearance of rash or skin reactions. (5.8)

ADVERSE REACTIONS

Most common (Greater than or equal to 5% and greater than placebo) adverse events in adults are diarrhea, upper respiratory tract infections, dyspepsia, and influenza-like symptoms (6.1) Adverse events observed in pediatric studies were similar in nature to the adult clinical trial experience (6.1) To report SUSPECTED ADVERSE REACTIONS, contact Boehringer Ingelheim Pharmaceuticals, Inc. at (800) 542-6257 or (800) 459-9906 TTY or FDA at 1-800-FDA-1088 or www.fda.gov/medwatch.

DRUG INTERACTIONS

Concomitant use of MOBIC and warfarin may result in increased risk of bleeding complications (7.7) Concomitant use of MOBIC and aspirin is not generally recommended because of the potential of increased adverse effect including increased GI bleeding (7.2) Concomitant use with MOBIC increases lithium plasma levels (7.4) Concomitant use with NSAIDs may reduce the antihypertensive effect of ACE-inhibitors (7.1)

USE IN SPECIFIC POPULATIONS

Based on animal data, may cause fetal harm. Starting at 30 weeks gestation, MOBIC should be avoided as premature closure of the ductus arteriosus in the fetus may occur. (5.9, 8.1) Nursing Mothers: Use with caution, as meloxicam may be excreted in human milk (8.3) See 17 for PATIENT COUNSELING INFORMATION and the FDA-approved Medication Guide

2.1 General Instructions 2.3 Rheumatoid Arthritis

Enter highlights text here

FULL PRESCRIBING INFORMATION

WARNING:

RISK OF SERIOUS CARDIOVASCULAR and GASTROINTESTINAL EVENTS

Cardiovascular Risk Nonsteroidal anti-inflammatory drugs (NSAIDs) may cause an increased risk of serious cardiovascular (CV) thrombotic events, myocardial infarction, and stroke, which can be fatal. This risk may increase with duration of use. Patients with cardiovascular disease or risk factors for cardiovascular disease may be at greater risk [see Warnings and Precautions (5.1)]. MOBIC is contraindicated for the treatment of peri-operative pain in the setting of coronary artery bypass graft (CABG) surgery [see Contraindications (4.2) and Warnings and Precautions (5.1)]. Gastrointestinal Risk NSAIDs cause an increased risk of serious gastrointestinal (GI) adverse reactions including bleeding, ulceration, and perforation of the stomach or intestines, which can be fatal. These events can occur at any time during use and without warning symptoms. Elderly patients are at greater risk for serious gastrointestinal events [see Warnings and Precautions (5.2)].

1.1 Osteoarthritis (OA) 1.2 Rheumatoid Arthritis (RA) 1.3 Juvenile Rheumatoid Arthritis (JRA) Pauciarticular and Polyarticular Course

1 INDICATIONS AND USAGE
1.1 Osteoarthritis (OA) MOBIC is indicated for relief of the signs and symptoms of osteoarthritis [see Clinical Studies (14.1)].
1.2 Rheumatoid Arthritis (RA) MOBIC is indicated for relief of the signs and symptoms of rheumatoid arthritis [see Clinical Studies (14.1)].
1.3 Juvenile Rheumatoid Arthritis (JRA) Pauciarticular and Polyarticular Course MOBIC is indicated for relief of the signs and symptoms of pauciarticular or polyarticular course Juvenile Rheumatoid Arthritis in patients 2 years of age and older [see Clinical Studies (14.2)].

2.1 General Instructions 2.3 Rheumatoid Arthritis

2 DOSAGE AND ADMINISTRATION

2.1 General Instructions Carefully consider the potential benefits and risks of MOBIC and other treatment options before deciding to use MOBIC. Use the lowest effective dose for the shortest duration consistent with individual patient treatment goals [see Warnings and Precautions (5.4)]. After observing the response to initial therapy with MOBIC, adjust the dose to suit an individual patient's needs. In adults, the maximum recommended daily oral dose of MOBIC is 15 mg regardless of formulation. In patients with hemodialysis, a maximum daily dosage of 7.5 mg is recommended [see Warnings and Precautions (5.6), Use in Specific Populations (8.7), and Clinical Pharmacology (12.3)]. MOBIC oral suspension 7.5 mg/5 mL or 15 mg/10 mL may be substituted for MOBIC tablets 7.5 mg or 15 mg, respectively. Shake the oral suspension gently before using. MOBIC may be taken without regard to timing of meals.

2.2 Osteoarthritis For the relief of the signs and symptoms of osteoarthritis the recommended starting and maintenance oral dose of MOBIC is 7.5 mg once daily. Some patients may receive additional benefit by increasing the dose to 15 mg once daily.

2.3 Rheumatoid Arthritis For the relief of the signs and symptoms of rheumatoid arthritis, the recommended starting and maintenance oral dose of MOBIC is 7.5 mg once daily. Some patients may receive additional benefit by increasing the dose to 15 mg once daily.

2.4 Juvenile Rheumatoid Arthritis (JRA) Pauciarticular and Polyarticular Course To improve dosing accuracy in smaller weight children, the use of the MOBIC oral suspension is recommended. MOBIC oral suspension is available in the strength of 7.5 mg/5 mL. For the treatment of juvenile rheumatoid arthritis, the recommended oral dose of MOBIC is 0.125 mg/kg once daily up to a maximum of 7.5 mg. There was no additional benefit demonstrated by increasing the dose above 0.125 mg/kg once daily in these clinical trials. Juvenile Rheumatoid Arthritis dosing using the oral suspension should be individualized based on the weight of the child:

0.125 mg/kg

Weight | Dose (1.5 mg/mL) | Delivered dose
12 kg (26 lb) | 1.0 mL | 1.5 mg
24 kg (54 lb) | 2.0 mL | 3.0 mg
36 kg (80 lb) | 3.0 mL | 4.5 mg
48 kg (106 lb | 4.0 mL | 6.0 mg
≥60 kg (132 lb) | 5.0 mL | 7.5 mg

3 DOSAGE FORMS AND STRENGTHS Tablets: 7.5 mg: pastel yellow, round, biconvex, uncoated tablet containing meloxicam 7.5 mg. Impressed with the Boehringer Ingelheim logo on one side and the letter “M” on the other. 15 mg: pastel yellow, oblong, biconvex, uncoated tablet containing meloxicam 15 mg. Impressed with the tablet code “15” on one side and the letter “M” on the other. Oral Suspension: yellowish green tinged viscous suspension containing 7.5 mg meloxicam in 5 mL.

4.1 Allergic Reactions 4.2 Coronary Surgery

4 CONTRAINDICATIONS
4.1 Allergic Reactions MOBIC is contraindicated in patients with known hypersensitivity (e.g., anaphylactoid reactions and serious skin reactions) to meloxicam. MOBIC should not be given to patients who have experienced asthma, urticaria, or allergic-type reactions after taking aspirin or other NSAIDs. Severe, rarely fatal, anaphylactic-like reactions to NSAIDs have been reported in such patients [see Warnings and Precautions (5.7, 5.13)].
4.2 Coronary Surgery MOBIC is contraindicated for the treatment of peri-operative pain in the setting of coronary artery bypass graft (CABG) surgery [see Warnings and Precautions (5.1)].

5.1 Cardiovascular Thrombotic Events 5.2 Gastrointestinal (GI) Effects - Risk of GI Ulceration, Bleeding, and Perforation 5.3 Hepatic Effects 5.4 Hypertension 5.5 Congestive Heart Failure and Edema 5.6 Renal Effects 5.7 Anaphylactoid Reactions 5.8 Adverse Skin Reactions 5.9 Pregnancy 5.12 Hematological Effects 5.13 Use in Patients with Pre-existing Asthma

5 WARNINGS AND PRECAUTIONS

5.1 Cardiovascular Thrombotic Events Clinical trials of several COX-2 selective and nonselective NSAIDs of up to three years’ duration have shown an increased risk of serious cardiovascular (CV) thrombotic events, myocardial infarction, and stroke, which can be fatal. All NSAIDs, both COX-2 selective and nonselective, may have a similar risk. Patients with known CV disease or risk factors for CV disease may be at greater risk. To minimize the potential risk for an adverse CV event in patients treated with an NSAID, the lowest effective dose should be used for the shortest duration possible. Physicians and patients should remain alert for the development of such events, even in the absence of previous CV symptoms. Patients should be informed about the signs and/or symptoms of serious CV events and the steps to take if they occur. Two large, controlled, clinical trials of a COX-2 selective NSAID for the treatment of pain in the first 10 to 14 days following CABG surgery found an increased incidence of myocardial infarction and stroke [see Contraindications (4.2)]. There is no consistent evidence that concurrent use of aspirin mitigates the increased risk of serious CV thrombotic events associated with NSAID use. The concurrent use of aspirin and an NSAID does increase the risk of serious GI events [see Warnings and Precautions (5.2)].

5.2 Gastrointestinal (GI) Effects - Risk of GI Ulceration, Bleeding, and Perforation NSAIDs, including MOBIC, can cause serious gastrointestinal (GI) adverse events including inflammation, bleeding, ulceration, and perforation of the stomach, small intestine, or large intestine, which can be fatal. These serious adverse events can occur at any time, with or without warning symptoms, in patients treated with NSAIDs. Only one in five patients who develop a serious upper GI adverse event on NSAID therapy is symptomatic. Upper GI ulcers, gross bleeding, or perforation caused by NSAIDs, occur in approximately 1% of patients treated for 3 to 6 months, and in about 2% to 4% of patients treated for one year. These trends continue with longer duration of use, increasing the likelihood of developing a serious GI event at some time during the course of therapy. However, even short-term therapy is not without risk. Prescribe NSAIDs, including MOBIC, with extreme caution in those with a prior history of ulcer disease or gastrointestinal bleeding. Patients with a prior history of peptic ulcer disease and/or gastrointestinal bleeding who use NSAIDs have a greater than 10-fold increased risk for developing a GI bleed compared to patients with neither of these risk factors. Other factors that increase the risk for GI bleeding in patients treated with NSAIDs include concomitant use of oral corticosteroids or anticoagulants, longer duration of NSAID therapy, smoking, use of alcohol, older age, and poor general health status. Most spontaneous reports of fatal GI events are in elderly or debilitated patients and therefore, special care should be taken in treating this population. To minimize the potential risk for an adverse GI event in patients treated with an NSAID, use the lowest effective dose for the shortest possible duration. Patients and physicians should remain alert for signs and symptoms of GI ulceration and bleeding during MOBIC therapy and promptly initiate additional evaluation and treatment if a serious GI adverse event is suspected. This should include discontinuation of MOBIC until a serious GI adverse event is ruled out. For high-risk patients, consider alternate therapies that do not involve NSAIDs.

5.3 Hepatic Effects Borderline elevations of one or more liver tests may occur in up to 15% of patients taking NSAIDs including MOBIC. These laboratory abnormalities may progress, may remain unchanged, or may be transient with continuing therapy. Notable elevations of ALT or AST (approximately three or more times the upper limit of normal) have been reported in approximately 1% of patients in clinical trials with NSAIDs. In addition, rare cases of severe hepatic reactions, including jaundice and fatal fulminant hepatitis, liver necrosis and hepatic failure, some of them with fatal outcomes have been reported [see Adverse Reactions (6.1)]. A patient with symptoms and/or signs suggesting liver dysfunction, or in whom an abnormal liver test has occurred, should be evaluated for evidence of the development of a more severe hepatic reaction while on therapy with MOBIC. If clinical signs and symptoms consistent with liver disease develop, or if systemic manifestations occur (e.g., eosinophilia, rash, etc.), discontinue MOBIC [see Use in Specific Populations (8.6) and Clinical Pharmacology (12.3)].

5.4 Hypertension NSAIDs, including MOBIC, can lead to onset of new hypertension or worsening of pre-existing hypertension, either of which may contribute to the increased incidence of CV events. NSAIDs, including MOBIC, should be used with caution in patients with hypertension. Blood pressure (BP) should be monitored closely during the initiation of NSAID treatment and throughout the course of therapy. Patients taking ACE inhibitors, thiazides, or loop diuretics may have impaired response to these therapies when taking NSAIDs.

5.5 Congestive Heart Failure and Edema Fluid retention and edema have been observed in some patients taking NSAIDs. Use MOBIC with caution in patients with fluid retention, hypertension, or heart failure.

5.6 Renal Effects Long-term administration of NSAIDs, including MOBIC, can result in renal papillary necrosis, renal insufficiency, acute renal failure, and other renal injury. Renal toxicity has also been seen in patients in whom renal prostaglandins have a compensatory role in the maintenance of renal perfusion. In these patients, administration of a nonsteroidal anti-inflammatory drug may cause a dose-dependent reduction in prostaglandin formation and, secondarily, in renal blood flow, which may precipitate overt renal decompensation. Patients at greatest risk of this reaction are those with impaired renal function, heart failure, liver dysfunction, those taking diuretics, ACE-inhibitors, and angiotensin II receptor antagonists, and the elderly. Discontinuation of NSAID therapy is usually followed by recovery to the pretreatment state. A pharmacokinetic study in patients with mild and moderate renal impairment revealed that no dosage adjustments in these patient populations are required. Patients with severe renal impairment have not been studied. The use of MOBIC in patients with severe renal impairment with CrCl less than 20 mL/min is not recommended. A study performed in patients on hemodialysis revealed that although overall Cmax was diminished in this population, the proportion of free drug not bound to plasma was increased. Therefore it is recommended that meloxicam dosage in this population not exceed 7.5 mg per day. Closely monitor the renal function of patients with impaired renal function who are taking MOBIC [see Dosage and Administration (2.1), Use in Specific Populations (8.7), and Clinical Pharmacology (12.3)]. Use caution when initiating treatment with MOBIC in patients with considerable dehydration. It is advisable to rehydrate patients first and then start therapy with MOBIC. Caution is also recommended in patients with pre-existing kidney disease. The extent to which metabolites may accumulate in patients with renal impairment has not been studied with MOBIC. Because some MOBIC metabolites are excreted by the kidney, monitor patients with significant renal impairment closely.

5.7 Anaphylactoid Reactions As with other NSAIDs, anaphylactoid reactions have occurred in patients without known prior exposure to MOBIC. MOBIC should not be given to patients with the aspirin triad. This symptom complex typically occurs in asthmatic patients who experience rhinitis with or without nasal polyps, or who exhibit severe, potentially fatal bronchospasm after taking aspirin or other NSAIDs [see Contraindications (4.1) and Warnings and Precautions (5.12)]. Seek emergency help in cases where an anaphylactoid reaction occurs.

5.8 Adverse Skin Reactions NSAIDs, including MOBIC, can cause serious skin adverse events such as exfoliative dermatitis, Stevens-Johnson Syndrome (SJS), and toxic epidermal necrolysis (TEN), which can be fatal. These serious events may occur without warning. Inform patients about the signs and symptoms of serious skin manifestations and discontinue use of the drug at the first appearance of skin rash or any other sign of hypersensitivity.

5.9 Pregnancy Starting at 30 weeks gestation, avoid the use of MOBIC because it may cause premature closure of the ductus arteriosus [see Use in Specific Populations (8.1) and Patient Counseling Information (17.8)].

5.10 Corticosteroid Treatment MOBIC cannot be expected to substitute for corticosteroids or to treat corticosteroid insufficiency. Abrupt discontinuation of corticosteroids may lead to disease exacerbation. Slowly taper patients on prolonged corticosteroid therapy if a decision is made to discontinue corticosteroids.

5.11 Masking of Inflammation and Fever The pharmacological activity of MOBIC in reducing fever and inflammation may diminish the utility of these diagnostic signs in detecting complications of presumed noninfectious, painful conditions.

5.12 Hematological Effects Anemia may occur in patients receiving NSAIDs, including MOBIC. This may be due to fluid retention, occult or gross GI blood loss, or an incompletely described effect upon erythropoiesis. Patients on long-term treatment with NSAIDs, including MOBIC, should have their hemoglobin or hematocrit checked if they exhibit any signs or symptoms of anemia. NSAIDs inhibit platelet aggregation and have been shown to prolong bleeding time in some patients. Unlike aspirin, their effect on platelet function is quantitatively less, of shorter duration, and reversible. Carefully monitor patients treated with MOBIC who may be adversely affected by alterations in platelet function, such as those with coagulation disorders or patients receiving anticoagulants.

5.13 Use in Patients with Pre-existing Asthma Patients with asthma may have aspirin-sensitive asthma. The use of aspirin in patients with aspirin-sensitive asthma has been associated with severe bronchospasm, which can be fatal. Since cross reactivity, including bronchospasm, between aspirin and other NSAIDs has been reported in such aspirin-sensitive patients, MOBIC should not be administered to patients with this form of aspirin sensitivity and should be used with caution in patients with pre-existing asthma.

5.14 Monitoring Because serious GI tract ulcerations and bleeding can occur without warning symptoms, physicians should monitor for signs or symptoms of GI bleeding. Patients on long-term treatment with NSAIDs should have their CBC and a chemistry profile checked periodically. If clinical signs and symptoms consistent with liver or renal disease develop, systemic manifestations occur (e.g., eosinophilia, rash, etc.) or if abnormal liver tests persist or worsen, MOBIC should be discontinued.

6.1 Clinical Trials Experience

6 ADVERSE REACTIONS

Because clinical trials are conducted under widely varying conditions, adverse reaction rates observed in the clinical trials of a drug cannot be directly compared to rates in the clinical trials of another drug and may not reflect the rates observed in practice. The following serious adverse reactions are discussed elsewhere in the labeling: Cardiovascular thrombotic events [see Boxed Warning and Warnings and Precautions (5.1)] Gastrointestinal effects – risk of GI ulceration, bleeding, and perforation [see Boxed Warning and Warnings and Precautions (5.2)] Hepatic effects [see Warnings and Precautions (5.3)] Hypertension [see Warnings and Precautions (5.4)] Congestive heart failure and edema [see Warnings and Precautions (5.5)] Renal effects [see Warnings and Precautions (5.6)] Anaphylactoid reactions [see Warnings and Precautions (5.7)] Adverse skin reactions [see Warnings and Precautions (5.8)] 6.1 Clinical Trials Experience Adults Osteoarthritis and Rheumatoid Arthritis The MOBIC Phase 2/3 clinical trial database includes 10,122 OA patients and 1012 RA patients treated with MOBIC 7.5 mg/day, 3505 OA patients and 1351 RA patients treated with MOBIC 15 mg/day. MOBIC at these doses was administered to 661 patients for at least 6 months and to 312 patients for at least one year. Approximately 10,500 of these patients were treated in ten placebo- and/or active-controlled osteoarthritis trials and 2363 of these patients were treated in ten placebo- and/or active-controlled rheumatoid arthritis trials. Gastrointestinal (GI) adverse events were the most frequently reported adverse events in all treatment groups across MOBIC trials. A 12-week multicenter, double-blind, randomized trial was conducted in patients with osteoarthritis of the knee or hip to compare the efficacy and safety of MOBIC with placebo and with an active control. Two 12-week multicenter, double-blind, randomized trials were conducted in patients with rheumatoid arthritis to compare the efficacy and safety of MOBIC with placebo. Table 1a depicts adverse events that occurred in greater than or equal to 2% of the MOBIC treatment groups in a 12-week placebo- and active-controlled osteoarthritis trial. Table 1b depicts adverse events that occurred in greater than or equal to 2% of the MOBIC treatment groups in two 12-week placebo-controlled rheumatoid arthritis trials.

Table 1a Adverse Events (%) Occurring in greater than or equal to 2% of MOBIC Patients in a 12-Week Osteoarthritis Placebo- and Active-Controlled Trial
 | Placebo | MOBIC 7.5 mg daily | MOBIC 15 mg daily | Diclofenac 100 mg daily
No. of Patients | 157 | 154 | 156 | 153
Gastrointestinal | 17.2 | 20.1 | 17.3 | 28.1
Abdominal pain | 2.5 | 1.9 | 2.6 | 1.3
Diarrhea | 3.8 | 7.8 | 3.2 | 9.2
Dyspepsia | 4.5 | 4.5 | 4.5 | 6.5
Flatulence | 4.5 | 3.2 | 3.2 | 3.9
Nausea | 3.2 | 3.9 | 3.8 | 7.2
Body as a Whole
Accident household | 1.9 | 4.5 | 3.2 | 2.6
Edema1 | 2.5 | 1.9 | 4.5 | 3.3
Fall | 0.6 | 2.6 | 0.0 | 1.3
Influenza-like symptoms | 5.1 | 4.5 | 5.8 | 2.6
Central and Peripheral Nervous System
Dizziness | 3.2 | 2.6 | 3.8 | 2.0
Headache | 10.2 | 7.8 | 8.3 | 5.9
Respiratory
Pharyngitis | 1.3 | 0.6 | 3.2 | 1.3
Upper respiratory tract infection | 1.9 | 3.2 | 1.9 | 3.3
Skin
Rash2 | 2.5 | 2.6 | 0.6 | 2.0

1 WHO preferred terms edema, edema dependent, edema peripheral, and edema legs combined 2 WHO preferred terms rash, rash erythematous, and rash maculo-papular combined

Table 1b Adverse Events (%) Occurring in greater than or equal to 2% of MOBIC Patients in two 12-Week Rheumatoid Arthritis Placebo-Controlled Trials
 | Placebo | MOBIC 7.5 mg daily | MOBIC 15 mg daily
No. of Patients | 469 | 481 | 477
Gastrointestinal Disorders | 14.1 | 18.9 | 16.8
Abdominal pain NOS2 | 0.6 | 2.9 | 2.3
Dyspeptic signs and symptoms1 | 3.8 | 5.8 | 4.0
Nausea2 | 2.6 | 3.3 | 3.8
General Disorders and Administration Site Conditions
Influenza-like illness2 | 2.1 | 2.9 | 2.3
Infection and Infestations
Upper respiratory tract infections-pathogen class unspecified1 | 4.1 | 7.0 | 6.5
Musculoskeletal and Connective Tissue Disorders
Joint related signs and symptoms1 | 1.9 | 1.5 | 2.3
Nervous System Disorders
Headaches NOS2 | 6.4 | 6.4 | 5.5
Skin and Subcutaneous Tissue Disorders
Rash NOS2 | 1.7 | 1.0 | 2.1

1 MedDRA high level term (preferred terms): dyspeptic signs and symptoms (dyspepsia, dyspepsia aggravated, eructation, gastrointestinal irritation), upper respiratory tract infections-pathogen unspecified (laryngitis NOS, pharyngitis NOS, sinusitis NOS), joint related signs and symptoms (arthralgia, arthralgia aggravated, joint crepitation, joint effusion, joint swelling) 2 MedDRA preferred term: nausea, abdominal pain NOS, influenza-like illness, headaches NOS, and rash NOS The adverse events that occurred with MOBIC in greater than or equal to 2% of patients treated short-term (4 to 6 weeks) and long-term (6 months) in active-controlled osteoarthritis trials are presented in Table 2.

Table 2 Adverse Events (%) Occurring in greater than or equal to 2% of MOBIC Patients in 4 to 6 Weeks and 6 Month Active-Controlled Osteoarthritis Trials
 | 4 to 6 Weeks Controlled Trials | 4 to 6 Weeks Controlled Trials | 6 Month Controlled Trials | 6 Month Controlled Trials
 | MOBIC 7.5 mg daily | MOBIC 15 mg daily | MOBIC 7.5 mg daily | MOBIC 15 mg daily
No. of Patients | 8955 | 256 | 169 | 306
Gastrointestinal | 11.8 | 18.0 | 26.6 | 24.2
Abdominal pain | 2.7 | 2.3 | 4.7 | 2.9
Constipation | 0.8 | 1.2 | 1.8 | 2.6
Diarrhea | 1.9 | 2.7 | 5.9 | 2.6
Dyspepsia | 3.8 | 7.4 | 8.9 | 9.5
Flatulence | 0.5 | 0.4 | 3.0 | 2.6
Nausea | 2.4 | 4.7 | 4.7 | 7.2
Vomiting | 0.6 | 0.8 | 1.8 | 2.6
Body as a Whole
Accident household | 0.0 | 0.0 | 0.6 | 2.9
Edema1 | 0.6 | 2.0 | 2.4 | 1.6
Pain | 0.9 | 2.0 | 3.6 | 5.2
Central and Peripheral Nervous System
Dizziness | 1.1 | 1.6 | 2.4 | 2.6
Headache | 2.4 | 2.7 | 3.6 | 2.6
Hematologic
Anemia | 0.1 | 0.0 | 4.1 | 2.9
Musculoskeletal
Arthralgia | 0.5 | 0.0 | 5.3 | 1.3
Back pain | 0.5 | 0.4 | 3.0 | 0.7
Psychiatric
Insomnia | 0.4 | 0.0 | 3.6 | 1.6
Respiratory
Coughing | 0.2 | 0.8 | 2.4 | 1.0
Upper respiratory tract infection | 0.2 | 0.0 | 8.3 | 7.5
Skin
Pruritus | 0.4 | 1.2 | 2.4 | 0.0
Rash2 | 0.3 | 1.2 | 3.0 | 1.3
Urinary
Micturition frequency | 0.1 | 0.4 | 2.4 | 1.3
Urinary tract infection | 0.3 | 0.4 | 4.7 | 6.9

1 WHO preferred terms edema, edema dependent, edema peripheral, and edema legs combined 2 WHO preferred terms rash, rash erythematous, and rash maculo-papular combined Higher doses of MOBIC (22.5 mg and greater) have been associated with an increased risk of serious GI events; therefore, the daily dose of MOBIC should not exceed 15 mg. Pediatrics Pauciarticular and Polyarticular Course Juvenile Rheumatoid Arthritis (JRA) Three hundred and eighty-seven patients with pauciarticular and polyarticular course JRA were exposed to MOBIC with doses ranging from 0.125 to 0.375 mg/kg per day in three clinical trials. These studies consisted of two 12-week multicenter, double-blind, randomized trials (one with a 12-week open-label extension and one with a 40-week extension) and one 1-year open-label PK study. The adverse events observed in these pediatric studies with MOBIC were similar in nature to the adult clinical trial experience, although there were differences in frequency. In particular, the following most common adverse events, abdominal pain, vomiting, diarrhea, headache, and pyrexia, were more common in the pediatric than in the adult trials. Rash was reported in seven (less than 2%) patients receiving MOBIC. No unexpected adverse events were identified during the course of the trials. The adverse events did not demonstrate an age or gender-specific subgroup effect. The following is a list of adverse drug reactions occurring in less than 2% of patients receiving MOBIC in clinical trials involving approximately 16,200 patients.

Body as a Whole | allergic reaction, face edema, fatigue, fever, hot flushes, malaise, syncope, weight decrease, weight increase
Cardiovascular | angina pectoris, cardiac failure, hypertension, hypotension, myocardial infarction, vasculitis
Central and Peripheral Nervous System | convulsions, paresthesia, tremor, vertigo
Gastrointestinal | colitis, dry mouth, duodenal ulcer, eructation, esophagitis, gastric ulcer, gastritis, gastroesophageal reflux, gastrointestinal hemorrhage, hematemesis, hemorrhagic duodenal ulcer, hemorrhagic gastric ulcer, intestinal perforation, melena, pancreatitis, perforated duodenal ulcer, perforated gastric ulcer, stomatitis ulcerative
Heart Rate and Rhythm | arrhythmia, palpitation, tachycardia
Hematologic | leukopenia, purpura, thrombocytopenia
Liver and Biliary System | ALT increased, AST increased, bilirubinemia, GGT increased, hepatitis
Metabolic a nd Nutritional | dehydration
Psychiatric | abnormal dreaming, anxiety, appetite increased, confusion, depression, nervousness, somnolence
Respiratory | asthma, bronchospasm, dyspnea
Skin and Appendages | alopecia, angioedema, bullous eruption, photosensitivity reaction, pruritus, sweating increased, urticaria
Special Senses | abnormal vision, conjunctivitis, taste perversion, tinnitus
Urinary System | albuminuria, BUN increased, creatinine increased, hematuria, renal failure

6.2 Post Marketing Experience The following adverse reactions have been identified during post approval use of MOBIC. Because these reactions are reported voluntarily from a population of uncertain size, it is not always possible to reliably estimate their frequency or establish a causal relationship to drug exposure. Decisions about whether to include an adverse event from spontaneous reports in labeling are typically based on one or more of the following factors: (1) seriousness of the event, (2) number of reports, or (3) strength of causal relationship to the drug. Adverse reactions reported in worldwide post marketing experience or the literature include: acute urinary retention; agranulocytosis; alterations in mood (such as mood elevation); anaphylactoid reactions including shock; erythema multiforme; exfoliative dermatitis; interstitial nephritis; jaundice; liver failure; Stevens-Johnson syndrome, and toxic epidermal necrolysis.

7.1 ACE-inhibitors 7.2 Aspirin 7.4 Lithium 7.5 Methotrexate 7.7 Warfarin

7 DRUG INTERACTIONS See also Clinical Pharmacology (12.3).

7.1 ACE-inhibitors NSAIDs may diminish the antihypertensive effect of ACE-inhibitors. This interaction should be given consideration in patients taking MOBIC concomitantly with ACE-inhibitors.

7.2 Aspirin When MOBIC is administered with aspirin (1000 mg three times daily) to healthy volunteers, an increase in the AUC (10%) and Cmax (24%) of meloxicam was noted. The clinical significance of this interaction is not known; however, as with other NSAIDs concomitant administration of meloxicam and aspirin is not generally recommended because of the potential for increased adverse effects. Concomitant administration of low-dose aspirin with MOBIC may result in an increased rate of GI ulceration or other complications, compared to use of MOBIC alone. MOBIC is not a substitute for aspirin for cardiovascular prophylaxis.

7.3 Diuretics Clinical studies, as well as post marketing observations, have shown that NSAIDs can reduce the natriuretic effect of furosemide and thiazides in some patients. This response has been attributed to inhibition of renal prostaglandin synthesis. However, studies with furosemide agents and meloxicam have not demonstrated a reduction in natriuretic effect. Furosemide single and multiple dose pharmacodynamics and pharmacokinetics are not affected by multiple doses of meloxicam. Nevertheless, during concomitant therapy with MOBIC, patients should be observed closely for signs of renal failure [see Warnings and Precautions (5.6)], as well as to ensure diuretic efficacy.

7.4 Lithium In a study conducted in healthy subjects, mean pre-dose lithium concentration and AUC were increased by 21% in subjects receiving lithium doses ranging from 804 to 1072 mg twice daily with meloxicam 15 mg every day as compared to subjects receiving lithium alone. These effects have been attributed to inhibition of renal prostaglandin synthesis by MOBIC. Closely monitor patients on lithium treatment for signs of lithium toxicity when MOBIC is introduced, adjusted, or withdrawn.

7.5 Methotrexate NSAIDs have been reported to competitively inhibit methotrexate accumulation in rabbit kidney slices. Therefore, NSAIDs may reduce the elimination of methotrexate, thereby enhancing the toxicity of methotrexate. Use caution when MOBIC is administered concomitantly with methotrexate [see Clinical Pharmacology (12.3)].

7.6 Cyclosporine MOBIC, like other NSAIDs, may affect renal prostaglandins, thereby altering the renal toxicity of certain drugs. Therefore, concomitant therapy with MOBIC may increase cyclosporine's nephrotoxicity. Use caution when MOBIC is administered concomitantly with cyclosporine.

7.7 Warfarin The effects of warfarin and NSAIDs on GI bleeding are synergistic, such that users of both drugs together have a risk of serious GI bleeding higher than users of either drug alone. Monitor anticoagulant activity, particularly in the first few days after initiating or changing MOBIC therapy in patients receiving warfarin or similar agents, since these patients are at an increased risk of bleeding than with the use of either drug alone. Use caution when administering MOBIC with warfarin since patients on warfarin may experience changes in INR and an increased risk of bleeding complications when a new medication is introduced [see Clinical Pharmacology (12.3)].

8.1 Pregnancy 8.7 Renal Impairment

8 USE IN SPECIFIC POPULATIONS

8.1 Pregnancy Pregnancy Category C; Category D starting 30 weeks gestation There are no adequate and well-controlled studies in pregnant women. Meloxicam crosses the placental barrier. Prior to 30 weeks gestation, use MOBIC during pregnancy only if the potential benefit justifies the potential risk to the fetus. Starting at 30 weeks gestation, avoid MOBIC and other NSAIDs, in pregnant women as premature closure of the ductus arteriosus in the fetus may occur. If this drug is used during this time period in pregnancy, inform the patient of the potential hazard to a fetus [see Warnings and Precautions (5.9) and Patient Counseling Information (17.8)]. Teratogenic Effects Meloxicam was not teratogenic when administered to pregnant rats during fetal organogenesis at oral doses up to 4 mg/kg/day (2.6-fold greater than the maximum recommended human daily dose [MRHD] based on body surface area [BSA] comparison). Administration of meloxicam to pregnant rabbits throughout embryogenesis produced an increased incidence of septal defects of the heart at an oral dose of 60 mg/kg/day. The no effect level was 20 mg/kg/day (26-fold greater than the MRHD based on BSA conversion) . Nonteratogenic Effects In rats and rabbits, embryolethality occurred at oral meloxicam doses of 1 mg/kg/day and 5 mg/kg/day, respectively (0.65- and 6.5- fold greater, respectively, than the MRHD based on BSA comparison) when administered throughout organogenesis.

LABOR AND DELIVERY

8.2 Labor and Delivery The effects of MOBIC on labor and delivery of pregnant women are unknown. Oral administration of meloxicam to pregnant rats during late gestation through lactation increased the incidence of dystocia, delayed parturition, and decreased offspring survival at meloxicam doses of 0.125 mg/kg/day or greater (at least 12.5 times lower than the maximum recommended human daily dose based on body surface area comparison).

8.3 Nursing Mothers It is not known whether this drug is excreted in human milk; however, meloxicam was excreted in the milk of lactating rats at concentrations higher than those in plasma. Because many drugs are excreted in human milk and because of the potential for serious adverse reactions in nursing infants from MOBIC, a decision should be made whether to discontinue nursing or to discontinue the drug, taking into account the importance of the drug to the mother.

PEDIATRIC USE

8.4 Pediatric Use The safety and effectiveness of meloxicam in pediatric JRA patients from 2 to 17 years of age has been evaluated in three clinical trials [see Dosage and Administration (2.3), Adverse Reactions (6.1), and Clinical Studies (14.2)].

8.6 Hepatic Impairment 8.7 Renal Impairment

8.5 Geriatric Use As with any NSAID, caution should be exercised in treating the elderly (65 years and older). Of the total number of subjects in clinical studies, 5157 were age 65 and over (4044 in OA studies and 1113 in RA studies). No overall differences in safety or effectiveness were observed between these subjects and younger subjects, and other reported clinical experience has not identified differences in responses between the elderly and younger patients, but greater sensitivity of some older individuals cannot be ruled out.
8.6 Hepatic Impairment No dose adjustment is necessary in patients with mild to moderate hepatic impairment. Patients with severe hepatic impairment have not been adequately studied. Since meloxicam is significantly metabolized in the liver; the use of meloxicam in these patients should be done with caution [see Warnings and Precautions (5.3) and Clinical Pharmacology (12.3)].
8.7 Renal Impairment No dose adjustment is necessary in patients with mild to moderate renal impairment. Patients with severe renal impairment have not been studied. The use of MOBIC in subjects with severe renal impairment is not recommended. Following a single dose of meloxicam, the free Cmax plasma concentrations were higher in patients with renal failure on chronic hemodialysis (1% free fraction) in comparison to healthy volunteers (0.3% free fraction). Therefore, it is recommended that meloxicam dosage in this population not exceed 7.5 mg per day. Hemodialysis did not lower the total drug concentration in plasma; therefore, additional doses are not necessary after hemodialysis. Meloxicam is not dialyzable [see Dosage and Administration (2.1), Warnings and Precautions (5.6), and Clinical Pharmacology (12.3)].

OVERDOSAGE

10 OVERDOSAGE There is limited experience with meloxicam overdose. Four cases have taken 6 to 11 times the highest recommended dose; all recovered. Cholestyramine is known to accelerate the clearance of meloxicam. Symptoms following acute NSAID overdose include lethargy, drowsiness, nausea, vomiting, and epigastric pain, which are generally reversible with supportive care. Gastrointestinal bleeding can occur. Severe poisoning may result in hypertension, acute renal failure, hepatic dysfunction, respiratory depression, coma, convulsions, cardiovascular collapse, and cardiac arrest. Anaphylactoid reactions have been reported with therapeutic ingestion of NSAIDs, and may occur following an overdose. Patients should be managed with symptomatic and supportive care following an NSAID overdose. Administration of activated charcoal is recommended for patients who present 1 to 2 hours after overdose. For substantial overdose or severely symptomatic patients, activated charcoal may be administered repeatedly. Accelerated removal of meloxicam by 4 gm oral doses of cholestyramine given three times a day was demonstrated in a clinical trial. Administration of cholestyramine may be useful following an overdose. Forced diuresis, alkalinization of urine, hemodialysis, or hemoperfusion may not be useful due to high protein binding. For additional information about overdose treatment, call a poison control center (1-800-222-1222).

DESCRIPTION

11 DESCRIPTION Meloxicam, an oxicam derivative, is a member of the enolic acid group of nonsteroidal anti-inflammatory drugs (NSAIDs). Each pastel yellow MOBIC tablet contains 7.5 mg or 15 mg meloxicam for oral administration. Each bottle of MOBIC oral suspension contains 7.5 mg meloxicam per 5 mL. Meloxicam is chemically designated as 4-hydroxy-2-methyl-N-(5-methyl-2-thiazolyl)-2H-1,2- benzothiazine-3-carboxamide-1,1-dioxide. The molecular weight is 351.4. Its empirical formula is C14H13N3O4S2 and it has the following structural formula:

Meloxicam is a pastel yellow solid, practically insoluble in water, with higher solubility observed in strong acids and bases. It is very slightly soluble in methanol. Meloxicam has an apparent partition coefficient (log P)app = 0.1 in n-octanol/buffer pH 7.4. Meloxicam has pKa values of 1.1 and 4.2. MOBIC is available as a tablet for oral administration containing 7.5 mg or 15 mg meloxicam, and as an oral suspension containing 7.5 mg meloxicam per 5 mL. The inactive ingredients in MOBIC tablets include colloidal silicon dioxide, crospovidone, lactose monohydrate, magnesium stearate, microcrystalline cellulose, povidone, and sodium citrate dihydrate. The inactive ingredients in MOBIC oral suspension include colloidal silicon dioxide, hydroxyethylcellulose, sorbitol, glycerol, xylitol, monobasic sodium phosphate (dihydrate), saccharin sodium, sodium benzoate, citric acid (monohydrate), raspberry flavor, and purified water.

CLINICAL PHARMACOLOGY

12 CLINICAL PHARMACOLOGY 12.1 Mechanism of Action The mechanism of action of meloxicam, like that of other NSAIDs, may be related to prostaglandin synthetase (cyclo-oxygenase) inhibition which is involved in the initial steps of the arachidonic acid cascade, resulting in the reduced formation of prostaglandins, thromboxanes and prostacylin. It is not completely understood how reduced synthesis of these compounds results in therapeutic efficacy.

PHARMACODYNAMICS

12.2 Pharmacodynamics Meloxicam exhibits anti-inflammatory, analgesic, and antipyretic activities.

12.3 Pharmacokinetics Absorption The absolute bioavailability of meloxicam capsules was 89% following a single oral dose of 30 mg compared with 30 mg IV bolus injection. Following single intravenous doses, dose-proportional pharmacokinetics were shown in the range of 5 mg to 60 mg. After multiple oral doses the pharmacokinetics of meloxicam capsules were dose-proportional over the range of 7.5 mg to 15 mg. Mean Cmax was achieved within four to five hours after a 7.5 mg meloxicam tablet was taken under fasted conditions, indicating a prolonged drug absorption. With multiple dosing, steady-state concentrations were reached by Day 5. A second meloxicam concentration peak occurs around 12 to 14 hours post-dose suggesting biliary recycling.

Meloxicam oral suspension doses of 7.5 mg/5 mL and 15 mg/10 mL have been found to be bioequivalent to meloxicam 7.5 mg and 15 mg capsules, respectively. Meloxicam capsules have been shown to be bioequivalent to MOBIC tablets.

Table 3 Single Dose and Steady-State Pharmacokinetic Parameters for Oral 7.5 mg and 15 mg Meloxicam (Mean and % CV)1
 |  | Steady State | Steady State | Steady State | Single Dose | Single Dose
Pharmacokinetic Parameters (% CV) |  | Healthy male adults (Fed)2 | Elderly males (Fed)2 | Elderly females (Fed)2 | Renal failure (Fasted) | Hepatic insufficiency (Fasted)
 |  | 7.5 mg3 tablets | 15 mg capsules | 15 mg capsules | 15 mg capsules | 15 mg capsules
N |  | 18 | 5 | 8 | 12 | 12
Cmax | [µg/mL] | 1.05(20) | 2.3 (59) | 3.2 (24) | 0.59 (36) | 0.84 (29)
tmax | [h] | 4.9 (8) | 5 (12) | 6 (27) | 4 (65) | 10 (87)
t1/2 | [h] | 20.1(29) | 21 (34) | 24 (34) | 18 (46) | 16 (29)
CL/f | [mL/min] | 8.8 (29) | 9.9 (76) | 5.1 (22) | 19 (43) | 11 (44)
Vz/f4 | [L] | 14.7(32) | 15 (42) | 10 (30) | 26 (44) | 14 (29)

1The parameter values in the table are from various studies 2 not under high fat conditions 3 MOBIC tablets 4 Vz/f =Dose/(AUC-Kel) Food and Antacid Effects Administration of meloxicam capsules following a high fat breakfast (75 g of fat) resulted in mean peak drug levels (i.e., Cmax) being increased by approximately 22% while the extent of absorption (AUC) was unchanged. The time to maximum concentration (Tmax) was achieved between 5 and 6 hours. In comparison, neither the AUC nor the Cmax values for meloxicam suspension were affected following a similar high fat meal, while mean Tmax values were increased to approximately 7 hours. No pharmacokinetic interaction was detected with concomitant administration of antacids. Based on these results, MOBIC can be administered without regard to timing of meals or concomitant administration of antacids. Distribution The mean volume of distribution (Vss) of meloxicam is approximately 10 L. Meloxicam is ~99.4% bound to human plasma proteins (primarily albumin) within the therapeutic dose range. The fraction of protein binding is independent of drug concentration, over the clinically relevant concentration range, but decreases to ~99% in patients with renal disease. Meloxicam penetration into human red blood cells, after oral dosing, is less than 10%. Following a radiolabeled dose, over 90% of the radioactivity detected in the plasma was present as unchanged meloxicam. Meloxicam concentrations in synovial fluid, after a single oral dose, range from 40% to 50% of those in plasma. The free fraction in synovial fluid is 2.5 times higher than in plasma, due to the lower albumin content in synovial fluid as compared to plasma. The significance of this penetration is unknown. Metabolism Meloxicam is extensively metabolized in the liver. Meloxicam metabolites include 5'-carboxy meloxicam (60% of dose), from P-450 mediated metabolism formed by oxidation of an intermediate metabolite 5'-hydroxymethyl meloxicam which is also excreted to a lesser extent (9% of dose). In vitro studies indicate that CYP2C9 (cytochrome P450 metabolizing enzyme) plays an important role in this metabolic pathway with a minor contribution of the CYP3A4 isozyme. Patients’ peroxidase activity is probably responsible for the other two metabolites which account for 16% and 4% of the administered dose, respectively. All the four metabolites are not known to have any in vivo pharmacological activity. Excretion Meloxicam excretion is predominantly in the form of metabolites, and occurs to equal extents in the urine and feces. Only traces of the unchanged parent compound are excreted in the urine (0.2%) and feces (1.6%). The extent of the urinary excretion was confirmed for unlabeled multiple 7.5 mg doses: 0.5%, 6%, and 13% of the dose were found in urine in the form of meloxicam, and the 5' hydroxymethyl and 5' carboxy metabolites, respectively. There is significant biliary and/or enteral secretion of the drug. This was demonstrated when oral administration of cholestyramine following a single IV dose of meloxicam decreased the AUC of meloxicam by 50%. The mean elimination half-life (t1/2) ranges from 15 hours to 20 hours. The elimination half-life is constant across dose levels indicating linear metabolism within the therapeutic dose range. Plasma clearance ranges from 7 to 9 mL/min. Special Populations Pediatric After single (0.25 mg/kg) dose administration and after achieving steady state (0.375 mg/kg/day), there was a general trend of approximately 30% lower exposure in younger patients (2 to 6 years old) as compared to the older patients (7 to 16 years old). The older patients had meloxicam exposures similar (single dose) or slightly reduced (steady state) to those in the adult patients, when using AUC values normalized to a dose of 0.25 mg/kg [see Dosage and Administration (2.2)]. The meloxicam mean (SD) elimination half-life was 15.2 (10.1) and 13.0 hours (3.0) for the 2 to 6 year old patients, and 7 to 16 year old patients, respectively. In a covariate analysis, utilizing population pharmacokinetics body-weight, but not age, was the single predictive covariate for differences in the meloxicam apparent oral plasma clearance. The body-weight normalized apparent oral clearance values were adequate predictors of meloxicam exposure in pediatric patients. The pharmacokinetics of MOBIC in pediatric patients under 2 years of age have not been investigated. Geriatric Elderly males (³65 years of age) exhibited meloxicam plasma concentrations and steady-state pharmacokinetics similar to young males. Elderly females (³65 years of age) had a 47% higher AUCss and 32% higher Cmax,ss as compared to younger females (£55 years of age) after body weight normalization. Despite the increased total concentrations in the elderly females, the adverse event profile was comparable for both elderly patient populations. A smaller free fraction was found in elderly female patients in comparison to elderly male patients. Gender Young females exhibited slightly lower plasma concentrations relative to young males. After single doses of 7.5 mg MOBIC, the mean elimination half-life was 19.5 hours for the female group as compared to 23.4 hours for the male group. At steady state, the data were similar (17.9 hours vs 21.4 hours). This pharmacokinetic difference due to gender is likely to be of little clinical importance. There was linearity of pharmacokinetics and no appreciable difference in the Cmax or Tmax across genders. Hepatic Impairment Following a single 15 mg dose of meloxicam there was no marked difference in plasma concentrations in patients with mild (Child- Pugh Class I) or moderate (Child-Pugh Class II) hepatic impairment compared to healthy volunteers. Protein binding of meloxicam was not affected by hepatic impairment. No dosage adjustment is necessary in patients with mild to moderate hepatic impairment. Patients with severe hepatic impairment (Child-Pugh Class III) have not been adequately studied [see Warnings and Precautions (5.3) and Use in Specific Populations (8.6)]. Renal Impairment Meloxicam pharmacokinetics have been investigated in subjects with mild and moderate renal impairment. Total drug plasma concentrations of meloxicam decreased and total clearance of meloxicam increased with the degree of renal impairment while free AUC values were similar in all groups. The higher meloxicam clearance in subjects with renal impairment may be due to increased fraction of unbound meloxicam which is available for hepatic metabolism and subsequent excretion. No dosage adjustment is necessary in patients with mild to moderate renal impairment. Patients with severe renal impairment have not been adequately studied. The use of MOBIC in subjects with severe renal impairment is not recommended [see Warnings and Precautions (5.6) and Use in Specific Populations (8.7)]. Hemodialysis Following a single dose of meloxicam, the free Cmax plasma concentrations were higher in patients with renal failure on chronic hemodialysis (1% free fraction) in comparison to healthy volunteers (0.3% free fraction). Hemodialysis did not lower the total drug concentration in plasma; therefore, additional doses are not necessary after hemodialysis. Meloxicam is not dialyzable [see Dosage and Administration (2.1), Warnings and Precautions (5.6), and Use in Specific Populations (8.7)]. Drug Interactions Aspirin: When MOBIC is administered with aspirin (1000 mg three times daily) to healthy volunteers, it tended to increase the AUC (10%) and Cmax (24%) of meloxicam. The clinical significance of this interaction is not known [see Drug Interactions (7.2)]. Cholestyramine: Pretreatment for four days with cholestyramine significantly increased the clearance of meloxicam by 50%. This resulted in a decrease in t1/2, from 19.2 hours to 12.5 hours, and a 35% reduction in AUC. This suggests the existence of a recirculation pathway for meloxicam in the gastrointestinal tract. The clinical relevance of this interaction has not been established. Cimetidine: Concomitant administration of 200 mg cimetidine four times daily did not alter the single-dose pharmacokinetics of 30 mg meloxicam. Digoxin: Meloxicam 15 mg once daily for 7 days did not alter the plasma concentration profile of digoxin after b-acetyldigoxin administration for 7 days at clinical doses. In vitro testing found no protein binding drug interaction between digoxin and meloxicam. Lithium: In a study conducted in healthy subjects, mean pre-dose lithium concentration and AUC were increased by 21% in subjects receiving lithium doses ranging from 804 to 1072 mg twice daily with meloxicam 15 mg QD every day as compared to subjects receiving lithium alone [see Drug Interactions (7.4)]. Methotrexate: A study in 13 rheumatoid arthritis (RA) patients evaluated the effects of multiple doses of meloxicam on the pharmacokinetics of methotrexate taken once weekly. Meloxicam did not have a significant effect on the pharmacokinetics of single doses of methotrexate. In vitro, methotrexate did not displace meloxicam from its human serum binding sites [see Drug Interactions (7.5)]. Warfarin: The effect of meloxicam on the anticoagulant effect of warfarin was studied in a group of healthy subjects receiving daily doses of warfarin that produced an INR (International Normalized Ratio) between 1.2 and 1.8. In these subjects, meloxicam did not alter warfarin pharmacokinetics and the average anticoagulant effect of warfarin as determined by prothrombin time. However, one subject showed an increase in INR from 1.5 to 2.1. Caution should be used when administering MOBIC with warfarin since patients on warfarin may experience changes in INR and an increased risk of bleeding complications when a new medication is introduced [see Drug Interactions (7.7)].

13 NONCLINICAL TOXICOLOGY

13.1 Carcinogenesis, Mutagenesis, Impairment of Fertility Carcinogenesis: There was no increase in tumor incidence in long-term carcinogenicity studies in rats (104 weeks) and mice (99 weeks) administered meloxicam at oral doses up to 0.8 mg/kg/day in rats and up to 8.0 mg/kg/day in mice (up to 0.5- and 2.6-fold, respectively, the maximum recommended human daily dose based on body surface area comparison). Mutagenesis: Meloxicam was not mutagenic in an Ames assay, or clastogenic in a chromosome aberration assay with human lymphocytes and an in vivo micronucleus test in mouse bone marrow. Impairment of Fertility: Meloxicam did not impair male and female fertility in rats at oral doses up to 9 mg/kg/day in males and 5 mg/ kg/day in females (up to 5.8- and 3.2-fold greater, respectively, than the maximum recommended human daily dose based on body surface area comparison).

14.1 Osteoarthritis and Rheumatoid Arthritis 14.2 Juvenile Rheumatoid Arthritis (JRA) Pauciarticular and Polyarticular Course

14 CLINICAL STUDIES

14.1 Osteoarthritis and Rheumatoid Arthritis The use of MOBIC for the treatment of the signs and symptoms of osteoarthritis of the knee and hip was evaluated in a 12-week, double-blind, controlled trial. MOBIC (3.75 mg, 7.5 mg, and 15 mg daily) was compared to placebo. The four primary endpoints were investigator’s global assessment, patient global assessment, patient pain assessment, and total WOMAC score (a self-administered questionnaire addressing pain, function, and stiffness). Patients on MOBIC 7.5 mg daily and MOBIC 15 mg daily showed significant improvement in each of these endpoints compared with placebo. The use of MOBIC for the management of signs and symptoms of osteoarthritis was evaluated in six double-blind, active-controlled trials outside the U.S. ranging from 4 weeks’ to 6 months’ duration. In these trials, the efficacy of MOBIC, in doses of 7.5 mg/day and 15 mg/day, was comparable to piroxicam 20 mg/day and diclofenac SR 100 mg/day and consistent with the efficacy seen in the U.S. trial. The use of MOBIC for the treatment of the signs and symptoms of rheumatoid arthritis was evaluated in a 12-week, double-blind, controlled multinational trial. MOBIC (7.5 mg, 15 mg, and 22.5 mg daily) was compared to placebo. The primary endpoint in this study was the ACR20 response rate, a composite measure of clinical, laboratory, and functional measures of RA response. Patients receiving MOBIC 7.5 mg and 15 mg daily showed significant improvement in the primary endpoint compared with placebo. No incremental benefit was observed with the 22.5 mg dose compared to the 15 mg dose. 14.2 Juvenile Rheumatoid Arthritis (JRA) Pauciarticular and Polyarticular Course The use of MOBIC for the treatment of the signs and symptoms of pauciarticular or polyarticular course Juvenile Rheumatoid Arthritis in patients 2 years of age and older was evaluated in two 12-week, double-blind, parallel-arm, active-controlled trials. Both studies included three arms: naproxen and two doses of meloxicam. In both studies, meloxicam dosing began at 0.125 mg/kg/day (7.5 mg maximum) or 0.25 mg/kg/day (15 mg maximum), and naproxen dosing began at 10 mg/kg/day. One study used these doses throughout the 12-week dosing period, while the other incorporated a titration after 4 weeks to doses of 0.25 mg/kg/day and 0.375 mg/ kg/day (22.5 mg maximum) of meloxicam and 15 mg/kg/day of naproxen. The efficacy analysis used the ACR Pediatric 30 responder definition, a composite of parent and investigator assessments, counts of active joints and joints with limited range of motion, and erythrocyte sedimentation rate. The proportion of responders were similar in all three groups in both studies, and no difference was observed between the meloxicam dose groups.

HOW SUPPLIED

16 HOW SUPPLIED/STORAGE AND HANDLING MOBIC is available as a pastel yellow, round, biconvex, uncoated tablet containing meloxicam 7.5 mg or as a pastel yellow, oblong, biconvex, uncoated tablet containing meloxicam 15 mg. The 7.5 mg tablet is impressed with the Boehringer Ingelheim logo on one side, and on the other side, the letter “M”. The 15 mg tablet is impressed with the tablet code “15” on one side and the letter “M” on the other. MOBIC is also available as a yellowish green tinged viscous oral suspension containing 7.5 mg meloxicam in 5 mL. MOBIC tablets 7.5 mg: NDC 0597-0029-01; Bottles of 100 MOBIC tablets 15 mg: NDC 0597-0030-01; Bottles of 100 MOBIC oral suspension 7.5 mg/5 mL: NDC 0597-0034-01; Bottles of 100 mL

STORAGE AND HANDLING

Storage Store at 25°C (77°F); excursions permitted to 15°C-30°C (59°F-86°F). Keep MOBIC tablets in a dry place. Dispense tablets in a tight container. Keep oral suspension container tightly closed. Keep this and all medications out of the reach of children.

17 PATIENT COUNSELING INFORMATION 17.8 Effects During Pregnancy

17 PATIENT COUNSELING INFORMATION See FDA-approved Medication Guide Patients should be informed of the following information before initiating therapy with an NSAID and periodically during the course of ongoing therapy. 17.1 Medication Guide Inform patients of the availability of a Medication Guide for NSAIDs that accompanies each prescription dispensed, and instruct them to read the Medication Guide prior to using MOBIC.

17.2 Cardiovascular Effects NSAIDs including MOBIC may cause serious CV side effects, such as MI or stroke, which may result in hospitalization and even death. Although serious CV events can occur without warning symptoms, patients should be alert for the signs and symptoms of chest pain, shortness of breath, weakness, slurring of speech, and should ask for medical advice when observing any indicative sign or symptoms. Patients should be apprised of the importance of this follow-up [see Warnings and Precautions (5.1)].

17.3 Gastrointestinal Effects NSAIDs including MOBIC, can cause GI discomfort and, rarely, serious GI side effects, such as ulcers and bleeding, which may result in hospitalization and even death. Although serious GI tract ulcerations and bleeding can occur without warning symptoms, patients should be alert for the signs and symptoms of ulcerations and bleeding, and should ask for medical advice when observing any indicative sign or symptoms including epigastric pain, dyspepsia, melena, and hematemesis. Patients should be apprised of the importance of this follow-up [see Warnings and Precautions (5.2)].

17.4 Hepatotoxicity Inform patients of the warning signs and symptoms of hepatotoxicity (e.g., nausea, fatigue, lethargy, pruritus, jaundice, right upper quadrant tenderness, and "flu like" symptoms). If these occur, instruct patients to stop therapy and seek immediate medical therapy [see Warnings and Precautions (5.3)].

17.5 Adverse Skin Reactions NSAIDs including MOBIC, can cause serious skin side effects such as exfoliative dermatitis, Stevens-Johnson Syndrome (SJS), and toxic epidermal necrolysis (TEN), which may result in hospitalization and even death. Although serious skin reactions may occur without warning, patients should be alert for the signs and symptoms of skin rash and blisters, fever, or other signs of hypersensitivity such as itching, and should ask for medical advice when observing any indicative signs or symptoms. Advise patients to stop the drug immediately if they develop any type of rash and contact their physicians as soon as possible [see Warnings and Precautions (5.8)].

17.6 Weight Gain and Edema Advise patients to promptly report signs or symptoms of unexplained weight gain or edema to their physicians [see Warnings and Precautions (5.5)].

17.7 Anaphylactoid Reactions Inform patients of the signs of an anaphylactoid reaction (e.g., difficulty breathing, swelling of the face or throat). Instruct patients seek immediate emergency help [see Warnings and Precautions (5.7)].

17.8 Effects During Pregnancy Starting at 30 weeks gestation, MOBIC should be avoided as premature closure of the ductus arteriosus in the fetus may occur [see Warnings and Precautions (5.9) and Use in Specific Populations (8.1)]. Please address medical inquiries to (800) 542-6257 or (800) 459-9906 TTY. Distributed by: Boehringer Ingelheim Pharmaceuticals, Inc. Ridgefield, CT 06877 USA Licensed from: Boehringer Ingelheim International GmbH ©Copyright 2010 Boehringer Ingelheim International GmbH ALL RIGHTS RESERVED 10003990/06 OT1400GD2810 090340141-7 OT1407E

MEDICATION GUIDE

Medication Guide for Non-Steroidal Anti-Inflammatory Drugs (NSAIDs) (See the end of this Medication Guide for a list of prescription NSAID medicines.) What is the most important information I should know about medicines called Non-Steroidal Anti-Inflammatory Drugs (NSAIDs)? NSAID medicines may increase the chance of a heart attack or stroke that can lead to death. This chance increases: - with longer use of NSAID medicines - in people who have heart disease NSAID medicines should never be used right before or after a heart surgery called a "coronary artery bypass graft (CABG)." NSAID medicines can cause ulcers and bleeding in the stomach and intestines at any time during treatment. Ulcers and bleeding: - can happen without warning symptoms - may cause death The chance of a person getting an ulcer or bleeding increases with: - taking medicines called "corticosteroids" and "anticoagulants" - longer use - smoking - drinking alcohol - older age - having poor health NSAID medicines should only be used: - exactly as prescribed - at the lowest dose possible for your treatment - for the shortest time needed What are Non-Steroidal Anti-Inflammatory Drugs (NSAIDs)? NSAID medicines are used to treat pain and redness, swelling, and heat (inflammation) from medical conditions such as: - different types of arthritis - menstrual cramps and other types of short-term pain Who should not take a Non-Steroidal Anti-Inflammatory Drug (NSAID)? Do not take an NSAID medicine: - if you had an asthma attack, hives, or other allergic reaction with aspirin or any other NSAID medicine - for pain right before or after heart bypass surgery Tell your healthcare provider: - about all of your medical conditions. - about all of the medicines you take. NSAIDs and some other medicines can interact with each other and cause serious side effects. Keep a list of your medicines to show to your healthcare provider and pharmacist. - if you are pregnant. NSAID medicines should not be used by pregnant women late in their pregnancy. - if you are breastfeeding. Talk to your doctor. What are the possible side effects of Non-Steroidal Anti-Inflammatory Drugs (NSAIDs)? Serious side effects include: - heart attack - stroke - high blood pressure - heart failure from body swelling (fluid retention) - kidney problems including kidney failure - bleeding and ulcers in the stomach and intestine - low red blood cells (anemia) - life-threatening skin reactions - life-threatening allergic reactions - liver problems including liver failure - asthma attacks in people who have asthma Other side effects include: - stomach pain - constipation - diarrhea - gas - heartburn - nausea - vomiting - dizziness Get emergency help right away if you have any of the following symptoms: - shortness of breath or trouble breathing - chest pain - weakness in one part or side of your body - slurred speech - swelling of the face or throat Stop your NSAID medicine and call your healthcare provider right away if you have any of the following symptoms: - nausea - more tired or weaker than usual - itching - your skin or eyes look yellow - stomach pain - flu-like symptoms - vomit blood - there is blood in your bowel movement or it is black and sticky like tar - unusual weight gain - skin rash or blisters with fever - swelling of the arms and legs, hands and feet These are not all the side effects with NSAID medicines. Talk to your healthcare provider or pharmacist for more information about NSAID medicines. Call your doctor for medical advice about side effects. You may report side effects to FDA at 1-800-FDA-1088. Other information about Non-Steroidal Anti-Inflammatory Drugs (NSAIDs) - Aspirin is an NSAID medicine but it does not increase the chance of a heart attack. Aspirin can cause bleeding in the brain, stomach, and intestines. Aspirin can also cause ulcers in the stomach and intestines. - Some of these NSAID medicines are sold in lower doses without a prescription (over-the-counter). Talk to your healthcare provider before using over-the-counter NSAIDs for more than 10 days.

NSAID medicines that need a prescription
Generic Name | Tradename
Celecoxib | Celebrex
Diclofenac | Cataflam, Voltaren, Arthrotec (combined with misoprostol)
Diflunisal | Dolobid
Etodolac | Lodine, Lodine XL
Fenoprofen | Nalfon, Nalfon 200
Flurbiprofen | Ansaid
Ibuprofen | Motrin, Tab-Profen, Vicoprofen* (combined with hydrocodone), Combunox (combined with oxycodone)
Indomethacin | Indocin, Indocin SR, Indo-Lemmon, Indomethagan
Ketoprofen | Oruvail
Ketorolac | Toradol
Mefenamic Acid | Ponstel
Meloxicam | Mobic
Nabumetone | Relafen
Naproxen | Naprosyn, Anaprox, Anaprox DS, EC-Naprosyn, Naprelan, Naprapac (copackaged with lansoprazole)
Oxaprozin | Daypro
Piroxicam | Feldene
Sulindac | Clinoril
Tolmetin | Tolectin, Tolectin DS, Tolectin 600

Vicoprofen contains the same dose of ibuprofen as over-the-counter (OTC) NSAIDs, and is usually used for less than 10 days to treat pain. The OTC NSAID label warns that long term continuous use may increase the risk of heart attack or stroke. This Medication Guide has been approved by the U.S. Food and Drug Administration.

PACKAGE LABEL

NDC 0597-0029-01 ATTENTION DISPENSER: Disperse with separately provided Medication Guide. Mobic (meloxicam) tablets 7.5 mg 100 tablets Dosage: Read accompanying prescribing information. RX only Boehringer Ingelheim EXP. LOT

Store at 25 degree C (77 degree F); excursions permitted to 15 degree - 30 degree C (59 degree - 86 degree F.) Dispense in a tight container.Keep in a dry place. Keep out of reach of children. Mfd. by: Boehringer Ingelheim (BI) Promeco, S.A de C.V. Mexico City,Mexico Lic. from: BI Int'l GmbH Mkd. by: BI Pharmaceuticals, Inc. Ridgefield, CT 06877 USA C2009 BI Int'l GmbH L1411A

Trepadone (U.S. patent pending) capsules by oral administration. A specially formulated Medical Food product, consisting of a proprietary blend of amino acids, glucosamine, chondroitin sulfate, fish oil, and polyphenol ingredients in specific proportions, for the dietary management of the metabolic processes associated with pain disorders and inflammatory conditions. (PD) (IC), particularly diseases associated with joint pain. Must be administered under physician supervision.
Medical Foods
Medical Food products are often used in hospitals (e.g., for burn victims or kidney dialysis patients) and outside of a hospital setting under a physician’s care for the dietary management of diseases in patients with particular medical or metabolic needs due to their disease or condition. Congress defined "Medical Food" in the Orphan Drug Act and Amendments of 1988 as "a food which is formulated to be consumed or administered enterally [or orally] under the supervision of a physician and which is intended for the specific dietary management of a disease or condition for which distinctive nutritional requirements, based on recognized scientific principles, are established by medical evaluation." Medical Foods are complex formulated products, requiring sophisticated and exacting technology. Trepadone has been developed, manufactured, and labeled in accordance with both the statutory and the FDA regulatory definition of a Medical Food. Trepadone must be used while the patient is under the ongoing care of a physician.

PAIN DISORDERS (PD) INFLAMMATORY CONDITIONS (IC)
PD and IC as a Metabolic Deficiency Disease
A critical component of the definition of a Medical Food is the requirement for a distinctive nutritional deficiency. FDA scientists have proposed a physiologic definition of a distinctive nutritional deficiency as follows: “the dietary management of patients with specific diseases requires, in some instances, the ability to meet nutritional requirements that differ substantially from the needs of healthy persons. For example, in establishing the recommended dietary allowances for general, healthy population, the Food and Nutrition Board of the Institute of Medicine National Academy of Sciences, recognized that different or distinctive physiologic requirements may exist for certain persons with "special nutritional needs arising from metabolic disorders, chronic diseases, injuries, premature birth, other medical conditions and drug therapies. Thus, the distinctive nutritional needs associated with a disease reflects the total amount needed by a healthy person to support life or maintain homeostasis, adjusted for the distinctive changes in the nutritional needs of the patient as a result of the effects of the disease process on absorption, metabolism and excretion.” It was also proposed that in patients with certain disease states who respond to nutritional therapies, a physiologic deficiency of the nutrient is assumed to exist. For example, if a patient with pain disorders responds to a tryptophan formulation by decreasing perceived pain, a deficiency of tryptophan is assumed to exist.
Patients with pain disorders and inflammatory conditions are known to have nutritional deficiencies of tryptophan, choline, arginine, GABA, flavonoids, and certain antioxidants. Patients with pain disorders and inflammatory conditions frequently exhibit reduced plasma levels of tryptophan and GABA and have been shown to respond to oral administration of GABA, arginine, tryptophan, or a 5-hydoxytryptophan formulation. Research has shown that tryptophan, arginine or GABA reduced diets result in a fall of circulating tryptophan, arginine, and/or GABA. Patients with pain disorders frequently exhibit activation of the degradation pathways that increases the turnover of GABA, arginine and/or tryptophan leading to a reduced level of production of serotonin, GABA or nitric oxide for a given precursor blood level. Patients with pain disorders and inflammatory conditions are known to have nutritional deficiencies of glucosamine and chondroitin sulfate. Patients with pain disorders and inflammatory conditions frequently exhibit reduced plasma levels of glucosamine and chondroitin sulfate and have been shown to respond to oral administration of glucosamine and chondroitin sulfate formulation. Patients with pain disorders and inflammatory conditions are known to have nutritional deficiencies of prostaglandin precursors such as omega-3 free fatty acids. Patients with pain disorders and inflammatory conditions frequently exhibit reduced plasma levels of prostaglandin precursors and have been shown to respond to oral administration of prostaglandin precursors, such as the Omega-3 free fatty acids, particularly in the form of fish oils. Research has also shown that a genetic predisposition to accelerated degradation of prostaglandins can lead to increased precursor requirements in certain patients with pain disorders and inflammatory conditions.
Choline is required to fully potentiate acetylcholine synthesis by brain neurons. A deficiency of choline leads to reduced acetylcholine production by the neurons. Flavonoids potentiate the production of acetylcholine by the neurons thereby reducing pain. Diets deficient in flavonoid rich foods and choline result in inadequate flavonoid concentrations, impeding acetylcholine production in certain patients with pain disorders and/or inflammatory conditions. Acetylcholine in pre-synaptic ganglia is necessary for the production of serotonin and nitric oxide in post-synaptic ganglia. Provision of tryptophan, arginine, GABA, choline and flavonoids with antioxidants, in specific proportions can restore the production of beneficial serotonin, nitric oxide, and acetylcholine, thereby reducing the perception of pain and reducing inflammation. L-Histidine is known to produce brain histamine that stimulates production of ACTH.

PRODUCT DESCRIPTION
Primary Ingredients
Trepadone consists of a proprietary blend of amino acids, prostaglandin precursors in the form of omega-3 free fatty acids, glucosamine, chondroitin sulfate, cocoa, caffeine, cinnamon, and flavonoids in specific proportions. These ingredients fall into the category of Generally Regarded as Safe” (GRAS) as defined by the Food and Drug Administration (FDA) (Sections 201(s) and 409 of the Federal Food, Drug, and Cosmetic Act). A GRAS substance is distinguished from a food additive on the basis of the common knowledge about the safety of the substance for its intended use. The standard for an ingredient to achieve GRAS status requires not only technical demonstration of non-toxicity and safety, but also general recognition of safety through widespread usage and agreement of that safety by experts in the field. Many ingredients have been determined by the U.S. Food and Drug Administration (FDA) to be GRAS, and are listed as such by regulation, in Volume 21 Code of Federal Regulations (CFR) Sections 182, 184, and 186.
Amino Acids
Amino Acids are the building blocks of protein. All amino acids are GRAS listed as they have been ingested by humans for many thousands of years. The doses of the amino acids in Trepadone are equivalent to those found in the usual human diet. Patients with pain disorders may require an increased amount of certain amino acids that cannot be obtained from normal diet alone. Tryptophan, for example, is an obligatory amino acid. The body cannot make tryptophan and must obtain tryptophan from the diet. Tryptophan is needed to produce serotonin. Serotonin is required to reduce pain. Patients with pain disorders and inflammatory conditions have altered serotonin metabolism. Some patients with pain disorders and inflammatory conditions have a resistance to the use of tryptophan that is similar to the mechanism found in insulin resistance. Patients with pain disorders and inflammatory conditions cannot acquire sufficient tryptophan from the diet to alter the perception of pain and the inflammatory process without ingesting a prohibitively large amount of calories, particularly calories from protein.
Chondroitin Sulfate and Glucosamine
Chondroitin sulfate and glucosamine are the building blocks of joint cartilage and are GRAS listed as they have been ingested by humans for thousands of years. The doses of the chondroitin sulfate and glucosamine in Trepadone are equivalent to those found in the usual human diet. Patients with pain disorders, particularly of the joints, may require an increased amount of chondroitin sulfate and glucosamine that cannot be obtained from normal diet alone. Patients with pain disorders and inflammatory conditions, particularly of the joints have altered chondroitin sulfate and glucosamine metabolism. Some patients with pain disorders and inflammatory conditions of the joints have a resistance to the use of chondroitin sulfate and glucosamine. Patients with pain disorders and inflammatory conditions of the joints cannot acquire sufficient chondroitin sulfate and glucosamine from the diet to alter the pain and the inflammatory process of the joint without ingesting a prohibitively large amount of calories, particularly calories from protein.
Omega-3 Free Fatty Acids in the Form of Fish Oil
Omega-3 Free Fatty Acids in the Form of Fish Oil are the building blocks of prostaglandin precursors that control the inflammatory process. Omega-3 Free Fatty Acids in the Form of Fish Oil are GRAS listed as they have been ingested by humans for thousands of years. The doses of the Omega-3 Free Fatty Acids in the Form of Fish Oil in Trepadone are equivalent to those found in the usual human diet. Patients with pain disorders, particularly of the joints, may require an increased amount of Omega-3 Free Fatty Acids in the Form of Fish Oil that cannot be obtained from normal diet alone. Patients with pain disorders and inflammatory conditions, particularly of the joints have altered prostaglandin metabolism. Some patients with pain disorders and inflammatory conditions exhibit a resistance to the use of Omega-3 Free Fatty Acids in the Form of Fish Oil. Patients with pain disorders and inflammatory conditions of the joints cannot acquire sufficient Omega-3 Free Fatty Acids in the Form of Fish Oil from the diet to alter the pain and the inflammatory process of the joint without ingesting a prohibitively large amount of calories.
Flavonoids
Flavonoids are a group of phytochemical compounds found in all vascular plants including fruits and vegetables. They are a part of a larger class of compounds known as polyphenols. Many of the therapeutic or health benefits of colored fruits and vegetables, cocoa, red wine, and green tea are directly related to their flavonoid content. The specially formulated flavonoids found in Trepadone cannot be obtained from conventional foods in the necessary proportions to elicit a therapeutic response.
Other Ingredients
Trepadone contains the following inactive or other ingredients, as fillers, excipients, and colorings: magnesium stearate, microcrystalline cellulose, Maltodextrin NF, gelatin (as the capsule material).
Physical Description
Trepadone is a yellow to light brown powder. Trepadone contains L-Glutamine, L-Arginine, L-Histidine, and L-Serine, 5-Hydroxytryptophan as Griffonia Seed Extract, GABA, Choline Bitartrate, Cinnamon, Cocoa, Hydrolyzed Whey Protein, and Grape Seed Extract.

CLINICAL PHARMACOLOGY
Mechanism of Action
Trepadone acts by restoring and maintaining the balance of the neurotransmitters; GABA, nitric oxide, serotonin, and acetylcholine that are associated with pain disorders and inflammatory conditions. Trepadone stimulates the production ACTH to reduce inflammation. Trepadone stimulates the production prostaglandins to reduce inflammation. Trepadone stimulates the production joint cartilage.
Metabolism
The amino acids in Trepadone are primarily absorbed by the stomach and small intestines. All cells metabolize the amino acids in Trepadone. Circulating tryptophan, arginine and choline blood levels determine the production of serotonin, nitric oxide, and acetylcholine. The Omega-3 free fatty acids in Trepadone are primarily absorbed by the stomach and small intestines. Inflammatory cells metabolize the free fatty acids in Trepadone.
Excretion
Trepadone is not an inhibitor of cytochrome P450 1A2, 2C9, 2C19, 2D6, or 3A4. These isoenzymes are principally responsible for 95% of all detoxification of drugs, with CYP3A4 being responsible for detoxification of roughly 50% of drugs. Amino acids do not appear to have an effect on drug metabolizing enzymes. Free fatty acids, glucosamine, and chondroitin sulfate do not appear to have an effect on drug metabolizing enzymes

INDICATIONS FOR USE
Trepadone is intended for the clinical dietary management of the metabolic processes of pain disorders and inflammatory conditions, particularly those associated with joint pain.
CLINICAL EXPERIENCE
Administration of Trepadone has demonstrated significant reduction in symptoms of pain and inflammation in patients with acute and chronic pain when used for the dietary management of the metabolic processes associated with pain disorders and inflammatory conditions. Administration of Trepadone results in the induction and maintenance of pain relief in patients with pain disorders and inflammatory conditions associated with joint pain.

PRECAUTIONS AND CONTRAINDICATIONS
Trepadone is contraindicated in an extremely small number of patients with hypersensitivity to any of the nutritional components of Trepadone.

ADVERSE REACTIONS
Oral supplementation with L-tryptophan, L-arginine or choline at high doses up to 15 grams daily is generally well tolerated. The most common adverse reactions of higher doses — from 15 to 30 grams daily — are nausea, abdominal cramps, and diarrhea. Some patients may experience these symptoms at lower doses. The total combined amount of amino acids in each Trepadone capsule does not exceed 400 mg. The doses of chondroitin sulfate, glucosamine, and omega-3 free fatty acids are well tolerated. Large doses of free fatty acids can be associated with bleeding disorders.

DRUG INTERACTIONS
Trepadone does not directly influence the pharmacokinetics of prescription drugs. Clinical experience has shown that administration of Trepadone may allow for lowering the dose of coadministered drugs under physician supervision.

OVERDOSAGE

OVERDOSE
There is a negligible risk of overdose with Trepadone as the total dosage of amino acids in a one month supply (90 capsules) is less than 36 grams. Overdose symptoms may include diarrhea, weakness, and nausea. There is a negligible risk of overdose with Trepadone as the total dosage of glucosamine, chondroitin sulfate, and omega-3 free fatty acids in a one month supply (90 capsules) is less than 10 grams. Overdose symptoms may include diarrhea, weakness, and nausea.
POST-MARKETING SURVEILLANCE
Post-marketing surveillance has shown no serious adverse reactions. Reported cases of mild rash and itching may have been associated with allergies to Trepadone flavonoid ingredients, including cinnamon, cocoa, and chocolate. These reactions were transient in nature and subsided within 24 hours.

DOSAGE AND ADMINISTRATION
Recommended Administration
For the dietary management of the metabolic processes associated with pain disorders and inflammatory conditions, particularly joint pain. Take (2) capsules up to four times per day times daily or as directed by physician. As with most amino acid formulations Trepadone should be taken without food to increase the absorption of key ingredients.

How Supplied
Trepadone is supplied in green and yellow, size 0 capsules in bottles of 90 capsules.
Physician Supervision
Trepadone is a Medical Food product available by prescription only and must be used while the patient is under ongoing physician supervision.
U.S. patents pending.
Manufactured by Arizona Nutritional Supplements, Inc. Chandler AZ 85225
Distributed by Physician Therapeutics LLC, Los Angeles, CA 90077. www.ptlcentral.com
© Copyright 2003-2006, Physician Therapeutics LLC, all rights reserved
NDC # 68405-1003-02
NDC: 68405-1016-03

Storage
Store at room temperature, 59-86oF (15-30oC) Protect from light and moisture. Trepadone is supplied to physicians in a recyclable plastic bottle with a child-resistant cap.

PACKAGE LABEL

PHYSICIAN THERAPEUTICS TREPADONE Medical Food Rx only 90 Capsules Directions for use: Must be administered under medical supervision. For adults only. As a Medical Food, take two (2) capsules four times daily in between meals. For the dietary management of osteoarthritis, tendonitis, and joint pain. Contains no added sugar, starch, wheat, yeast, preservatives, or flavor. Storage: Keep tightly closed in a cool dry place 8-32 Degree Centigrade (45-90 Degree F), relative humidity, below 50%. Warning: Keep this product out of the reach of children. NDC#68405-1016-03 Ingredients: Each serving (per 2 capsules) contains: Proprietary Amino Acid Blend L-Histadine, GABA, Hydrolyzed Whey Protein Glucosamine Omega - 3 FFA from Tuna Oil Chondroitin Sulfate Grape Seed Extract Cocoa (6% Theobromine) (fruit) Other indgredients: Gelatin. tricalcium phosphate, magnesium stearate, silicon dioxide, microcrystalline cellulose, FD and C yello #5, FD and C yellow #6, chlorophyllin copper complex, titanium dioxide. Distributed by: Physician Therapeutics LLC, Los Angeles, CA 90077 www.ptlcentral.com Patent Pending

PACKAGE LABEL

For the Dietary Management of Joint Disorder.
Two capsules up to four times daily or as directed by physician. See product label and insert.
Trepadone Medical Food
PHYSICIAN THERAPEUTICS
Trepadone Meloxicam 7.5 mg
A Convenience Packed Medical Food and Drug
Trepoxicam - 7.5
PHYSICIAN THERAPEUTICS
Trepadone 90 Capsules
Meloxicam 7.5 mg 30 Tablets
No Refills Without Physician Authorization
Rx only
NDC# 68405-036-36 of this co-pack
As prescribed by physician. See product label and product information insert.
Meloxicam 7.5 mg
Rx Drug
Manufactured and Distributed by Physician Therapeutics, A Division of Targeted Medical Pharma Inc. Los Angeles, CA 90077 www.ptlcentral.com
B-NDC# 68405-8036-36